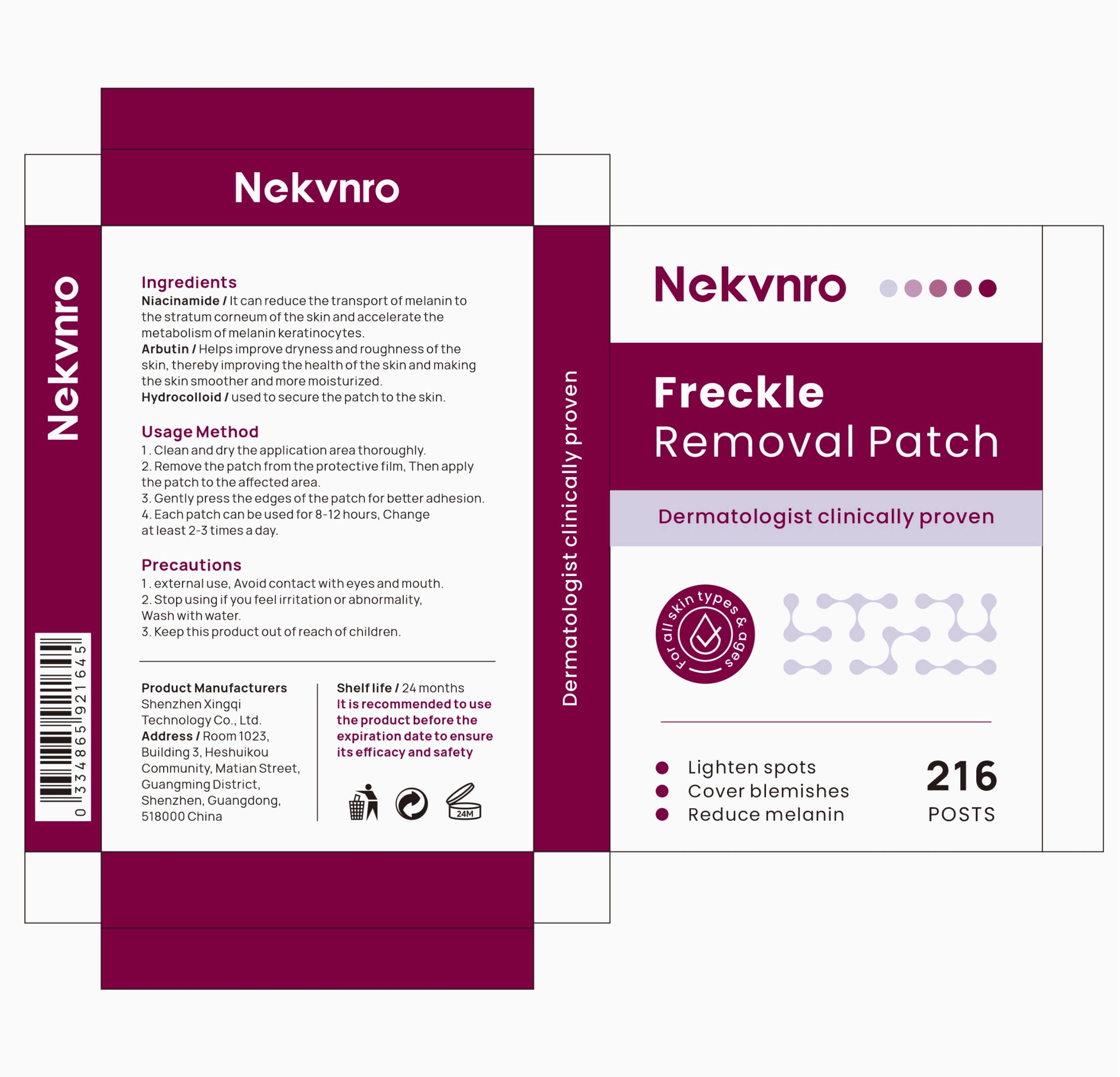 DRUG LABEL: Nekvnro Freckle Removal Patch
NDC: 84613-059 | Form: PATCH
Manufacturer: Shenzhen Xingqi Technology Co., Ltd.
Category: otc | Type: HUMAN OTC DRUG LABEL
Date: 20241010

ACTIVE INGREDIENTS: NIACINAMIDE 1 g/1 g; ARBUTIN 1 g/1 g
INACTIVE INGREDIENTS: SODIUM ALGINATE

ACTIVE INGREDIENT

Niacinamide 1%

Arbutin 1%

Purpose

Freckle Removal Patch

Uses

Usage Method
1.Clean and dry the application area thoroughly.
2. Remove the patch from the protective film, Then apply the patch to the affected area.
3. Gently press the edges of the patch for better adhesion.
4.Each patch can be used for 8-12 hours, Change at least 2-3 times a day.

Warnings

Precautions
1. external use, Avoid contact with eyes and mouth.
2. Stop using if you feel irritation or abnormality, Wash with water.
3. Keep this product out of reach ofchildren.

Dosage and administration

For external use only.

Do not use

1,external use, Avoid contact with eyes and mouth.
2,Stop using if you feel irritation or abnormality,Wash with water.
3,Keep this product out of reach of children.

When using section

1,external use, Avoid contact with eyes and mouth.
2,Stop using if you feel irritation or abnormality,Wash with water.
3,Keep this product out of reach of children.

stop use

1, external use,Avoid contact with eyes and mouth.
2，Stop using if you feel irritation or abnormality,Wash with water.
3， Keep this product out of reach of children.

KEEP OUT OF REACH OF CHILDREN SECTION

Keep this product out of reach of children.

Inactive ingredients

Hydrocolloid